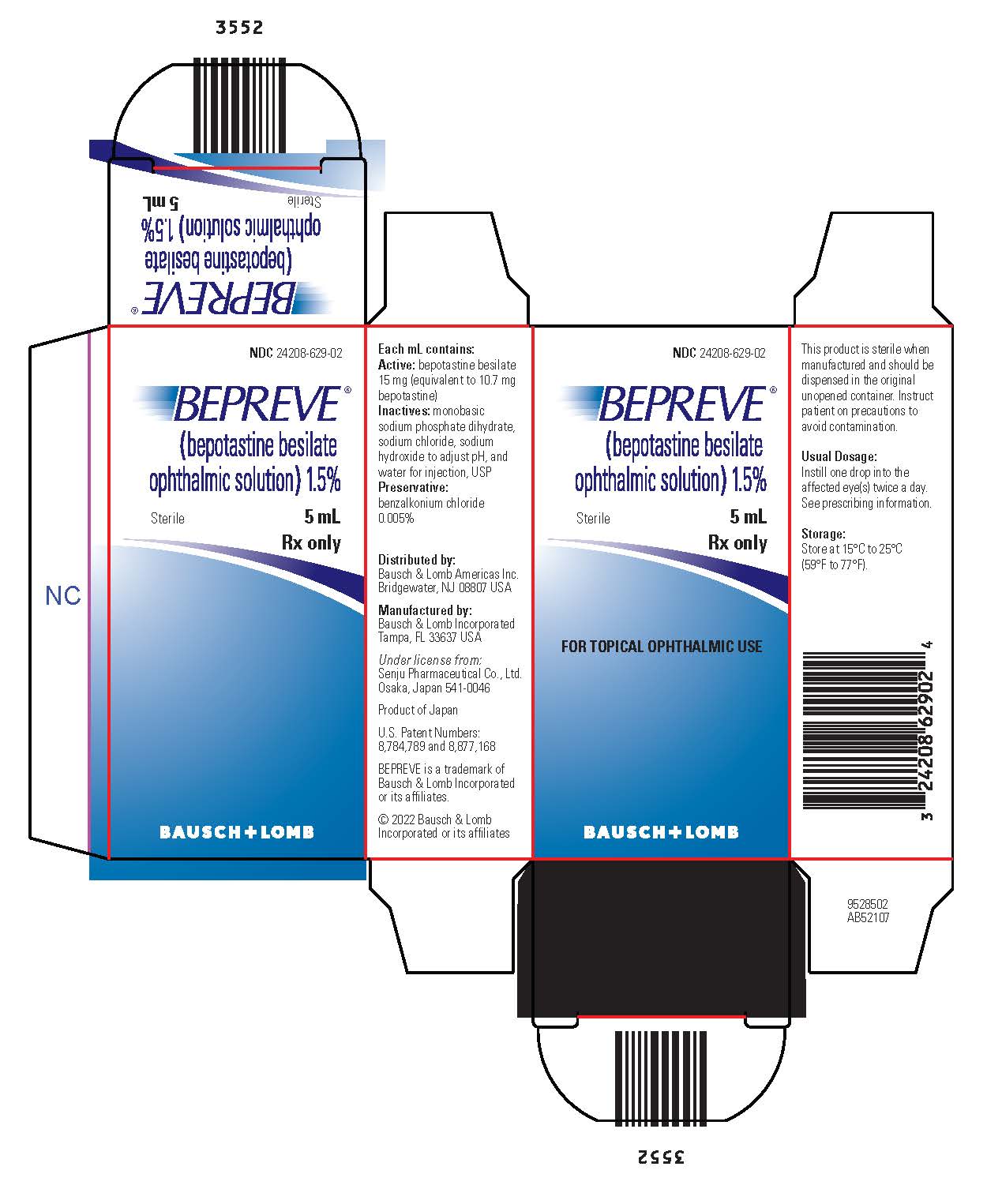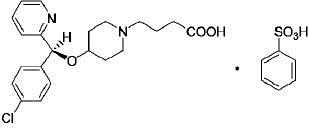 DRUG LABEL: Bepreve
NDC: 24208-629 | Form: SOLUTION/ DROPS
Manufacturer: Bausch & Lomb Incorporated
Category: prescription | Type: HUMAN PRESCRIPTION DRUG LABEL
Date: 20220831

ACTIVE INGREDIENTS: BEPOTASTINE BESYLATE 15 mg/1 mL
INACTIVE INGREDIENTS: BENZALKONIUM CHLORIDE 0.05 mg/1 mL; SODIUM PHOSPHATE, MONOBASIC, DIHYDRATE; SODIUM CHLORIDE; SODIUM HYDROXIDE; WATER

HIGHLIGHTS OF PRESCRIBING INFORMATION

These highlights do not include all the information needed to use BEPREVE safely and effectively. See full prescribing information for BEPREVE.
BEPREVE® (bepotastine besilate ophthalmic solution), for topical ophthalmic use
Initial U.S. Approval: 2009

1 INDICATIONS AND USAGE

BEPREVE is a histamine H1 receptor antagonist indicated for the treatment of itching associated with allergic conjunctivitis. (1)

2 DOSAGE AND ADMINISTRATION

- Instill one drop into the affected eye(s) twice a day. (2)
- Remove contact lenses prior to instillation of BEPREVE. (2)

3 DOSAGE FORMS AND STRENGTHS

Ophthalmic solution containing bepotastine besilate, 15 mg/mL (1.5%). (3)

4 CONTRAINDICATIONS

Hypersensitivity to any component of this product. (4)

5 WARNINGS AND PRECAUTIONS

- Contamination of Solution: Do not touch the dropper tip to any surface. Keep bottle tightly closed when not in use. (5.1)
- Contact Lens Wear: BEPREVE should not be used to treat contact lens-related irritation. (5.2)

6 ADVERSE REACTIONS

The most common adverse reaction occurring in approximately 25% of patients was a mild taste following instillation. Other adverse reactions which occurred in 2-5% of subjects were eye irritation, headache, and nasopharyngitis. (6.1)

To report SUSPECTED ADVERSE REACTIONS, contact Bausch & Lomb Incorporated at 1-800-553-5340 or FDA at 1-800-FDA-1088 or www.fda.gov/medwatch.

FULL PRESCRIBING INFORMATION

1 INDICATIONS AND USAGE

BEPREVE® (bepotastine besilate ophthalmic solution) 1.5% is a histamine H1 receptor antagonist indicated for the treatment of itching associated with signs and symptoms of allergic conjunctivitis.

2 DOSAGE AND ADMINISTRATION

Instill one drop of BEPREVE into the affected eye(s) twice a day. Remove contact lenses prior to instillation of BEPREVE.

3 DOSAGE FORMS AND STRENGTHS

Ophthalmic solution containing bepotastine besilate 15 mg/mL (1.5%).

4 CONTRAINDICATIONS

BEPREVE is contraindicated in patients with a history of hypersensitivity reactions to bepotastine or any of the other ingredients [see Adverse Reactions (6.2)].

5 WARNINGS AND PRECAUTIONS

5.1 Contamination of Tip and Solution

To minimize contaminating the dropper tip and solution, advise the patient not to touch the eyelids or surrounding areas with the dropper tip of the bottle and to keep the bottle tightly closed when not in use.

5.2 Contact Lens Wear

BEPREVE should not be used to treat contact lens-related irritation.

BEPREVE should not be instilled while wearing contact lenses. Patient should remove contact lenses prior to instillation of BEPREVE, because benzalkonium chloride may be absorbed by soft contact lenses. Lenses may be reinserted after 10 minutes following administration of BEPREVE.

6 ADVERSE REACTIONS

6.1 Clinical Trials Experience

Because clinical trials are conducted under widely varying conditions, adverse reaction rates observed in the clinical trials of a drug cannot be directly compared to rates in the clinical trials of another drug and may not reflect the rates observed in clinical practice.

The most common reported adverse reaction occurring in approximately 25% of subjects was a mild taste following instillation. Other adverse reactions occurring in 2-5% of subjects were eye irritation, headache, and nasopharyngitis.

6.2 Post-Marketing Experience

Hypersensitivity reactions have been reported rarely during the post-marketing use of BEPREVE. Because these reactions are reported voluntarily from a population of unknown size, it is not always possible to reliably estimate their frequency or establish a causal relationship to drug exposure. The hypersensitivity reactions may include itching, body rash, and swelling of lips, tongue and/or throat.

8 USE IN SPECIFIC POPULATIONS

8.1 Pregnancy

Risk Summary
There are no available human data for the use of BEPREVE during pregnancy to inform any drug-associated risks.

Oral administration of bepotastine besilate to pregnant rats or rabbits during organogenesis or during the pre/postnatal period did not produce adverse embryofetal or offspring effects at clinically relevant systemic exposures. Maternal toxicity was observed in the rabbits at the lowest dose administered, 20 mg/kg/day (215 times the maximum recommended human ophthalmic dose, RHOD, on a mg/m^2 basis) [see Data].

The background risk of major birth defects and miscarriage for the indicated population is unknown. However, the background risk in the U.S. general population of major birth defects is 2 to 4%, and of miscarriage is 15 to 20%, of clinically recognized pregnancies.

Data

Animal Data

In embryofetal development studies, oral administration of bepotastine besilate to pregnant rabbits throughout organogenesis did not produce teratogenic effects at maternal doses up to 500 mg/kg/day (approximately 5,400 times the maximum RHOD, on a mg/m^2 basis). A maternal no observed adverse effect level (NOAEL) was not identified in this study due to spontaneous abortion observed at the lowest dose tested, 20 mg/kg/day (approximately 215 times higher than

the maximum RHOD, on a mg/m^2 basis). Oral administration of bepotastine besilate to pregnant rats throughout organogenesis produced skeletal anomalies at 1,000 mg/kg/day (5,400 times higher than the maximum RHOD, on a mg/m^2 basis), a dose that also produced maternal toxicity and lethality. No teratogenic effects were observed in rats at maternal doses up to 200 mg/kg/day (corresponding to an estimated blood plasma concentration 3,300 times higher than that anticipated in humans at the maximum RHOD). A maternal NOAEL was observed at 10 mg/kg/day (54 times higher than the maximum RHOD, on a mg/m^2 basis). Following a single 3 mg/kg oral dose in rats (16 times higher than the maximum RHOD, on a mg/m^2 basis), the concentration of radio-labeled bepotastine besilate was similar in fetal liver and maternal blood plasma. The concentration in other fetal tissues was one-third to one-tenth the concentration in maternal blood plasma.

In a pre/postnatal development study, oral administration of bepotastine besilate to rats during the perinatal and lactation periods produced an increase in stillbirths and decreased growth and development in offspring at a maternal dose of 1,000 mg/kg/day (5,400 times higher than the maximum RHOD, on a mg/m^2 basis). There were no observed adverse effects on offspring of rats treated with 100 mg/kg/day (540 times higher than the maximum RHOD, on a mg/m^2 basis).

Effects on parturition and maternal lethality were observed at 100 mg/kg/day and 1,000 mg/kg/day, respectively. A maternal NOAEL was observed at 10 mg/kg/day (54 times higher than the maximum RHOD, on a mg/m^2 basis).

8.2 Lactation

Risk Summary

There are no data on the presence of BEPREVE in human milk, the effects on the breastfed infant or the effects on milk production.

The developmental and health benefits of breastfeeding should be considered, along with the mother’s clinical need for BEPREVE, and any potential adverse effects on the breastfed infant from BEPREVE.

Animal Data

Following a single 3 mg/kg oral dose (16 times the maximum RHOD, on a mg/m2 basis) of radio-labeled bepotastine besilate to nursing rats 11 days after delivery, the maximum concentration of radioactivity in milk was 0.40 mcg-eq/mL 1 hour after administration; at 48 hours after administration, the radioactivity concentration was below detection limits. The milk radioactivity concentration was higher than the maternal blood plasma radioactivity concentration at each time of measurement. It is not known whether bepotastine besilate would be present in maternal milk following topical ocular administration.

8.4 Pediatric Use

Safety and efficacy of BEPREVE (bepotastine besilate ophthalmic solution) 1.5% have not been established in pediatric patients under 2 years of age. Efficacy in pediatric patients under 10 years of age was extrapolated from clinical trials conducted in pediatric patients greater than 10 years of age and from adults.

8.5 Geriatric Use

No overall differences in safety or effectiveness have been observed between elderly and younger patients.

11 DESCRIPTION

BEPREVE (bepotastine besilate ophthalmic solution) 1.5% is a sterile, topically administered drug for ophthalmic use. Each mL of BEPREVE contains 15 mg bepotastine besilate. Bepotastine besilate is designated chemically as (+) -4-[[(S)-p-chloro-alpha -2-pyridylbenzyl]oxy]-1-piperidine butyric acid monobenzenesulfonate. The chemical structure for bepotastine besilate is:

Bepotastine besilate is a white to pale yellowish-white crystalline powder. The molecular weight of bepotastine besilate is 547.06 daltons. BEPREVE ophthalmic solution is supplied as a sterile, aqueous 1.5% solution, with an approximate pH of 6.8. The osmolality of BEPREVE (bepotastine besilate ophthalmic solution) 1.5% is approximately 295 mOsm/kg.

Each mL of BEPREVE (bepotastine besilate ophthalmic solution) 1.5% contains:

- Active: bepotastine besilate 15 mg (equivalent to 10.7 mg bepotastine)
- Inactives: monobasic sodium phosphate dihydrate, sodium chloride, sodium hydroxide to adjust pH, and water for injection, USP
- Preservative: benzalkonium chloride 0.005%

12 CLINICAL PHARMACOLOGY

12.1 Mechanism of Action

Bepotastine is a topically active, direct H1-receptor antagonist and an inhibitor of the release of histamine from mast cells.

12.3 Pharmacokinetics

Absorption: The extent of systemic exposure to bepotastine following topical ophthalmic administration of bepotastine besilate 1% and 1.5% ophthalmic solutions was evaluated in 12 healthy adults. Following one drop of 1% or 1.5% bepotastine besilate ophthalmic solution to both eyes four times daily (QID) for 7 days, bepotastine plasma concentrations peaked at approximately 1 to 2 hours post-instillation. Maximum plasma concentrations for the 1% and 1.5% strengths were 5.1 ± 2.5 ng/mL and 7.3 ± 1.9 ng/mL, respectively. Plasma concentrations at 24 hours post-instillation were below the quantifiable limit (2 ng/mL) in 11/12 subjects in the two dose groups.

Distribution: The extent of protein binding of bepotastine is approximately 55% and independent of bepotastine concentration.

Metabolism: In vitro metabolism studies with human liver microsomes demonstrated that bepotastine is minimally metabolized by CYP450 isozymes. In vitro studies demonstrated that bepotastine besilate does not inhibit the metabolism of various cytochrome P450 substrates via inhibition of CYP3A4, CYP2C9, and CYP2C19. The effect of bepotastine besilate on the metabolism of substrates of CYP1A2, CYP2C8, and CYP2D6 was not studied. Bepotastine besilate has a low potential for drug interaction via inhibition of CYP3A4, CYP2C9, and CYP2C19.

Excretion: The main route of elimination of bepotastine besilate is urinary excretion (with approximately 75-90% excreted unchanged in urine).

13 NONCLINICAL TOXICOLOGY

13.1 Carcinogenesis, Mutagenesis, Impairment of Fertility

Carcinogenesis

Long-term dietary studies in mice and rats were conducted to evaluate the carcinogenic potential of bepotastine besilate. Bepotastine besilate did not significantly induce neoplasms in mice receiving a nominal dose of up to 200 mg/kg/day for 21 months, or in rats receiving a nominal dose of up to 97 mg/kg/day for 24 months. These dose levels correspond to systemic exposures approximately 350 and 200 times higher than that achieved at the RHOD, respectively.

The no observable adverse effect level for bepotastine besilate based on nominal dose levels in carcinogenicity tests were 18.7 to 19.9 mg/kg/day in mice and 9.6 to 9.8 mg/kg/day in rats (corresponding to systemic exposures approximately 60 and 20 times higher than that anticipated in humans at RHOD, respectively).

Mutagenesis

There was no evidence of genotoxicity in the Ames test (mutagenicity), in CHO cells (chromosome aberration), in mouse hepatocytes (unscheduled DNA synthesis), or in the mouse micronucleus test.

Impairment of Fertility

Oral administration of bepotastine to male and female rats at doses up to 1,000 mg/kg/day (5,400 times higher than the maximum RHOD, on a mg/m^2 basis) resulted in reduction in fertility index and surviving fetuses. Oral administration of bepotastine besilate produced no observed adverse effects on fertility or reproduction in rats at oral doses up to 200 mg/kg/day (corresponding to an estimated blood plasma concentration 3,300 times higher than that anticipated in humans at the RHOD).

14 CLINICAL STUDIES

Clinical efficacy was evaluated in two conjunctival allergen challenge (CAC) studies (237 patients). BEPREVE (bepotastine besilate ophthalmic solution) 1.5% was more effective than its vehicle for relieving ocular itching induced by an ocular allergen challenge, both at a CAC 15 minutes post-dosing and a CAC 8 hours post-dosing of BEPREVE.

The safety of BEPREVE was evaluated in a randomized clinical study of 861 subjects over a period of 6 weeks.

16 HOW SUPPLIED/STORAGE AND HANDLING

BEPREVE (bepotastine besilate ophthalmic solution) 1.5% is supplied in a white low density polyethylene bottle with a sterile linear low density polyethylene controlled dropper tip and a white polypropylene cap in the following sizes:

NDC 24208-629-02 5 mL Bottle
NDC 24208-629-01 10 mL Bottle

Storage:

Store at 15°C to 25°C (59°F to 77°F).

17 PATIENT COUNSELING INFORMATION

- Sterility of Dropper Tip
Advise patients not to touch the dropper tip to any surface, as this may contaminate the solution and to keep the bottle tightly closed when not in use.

Distributed by:
Bausch & Lomb Americas Inc.
Bridgewater, NJ 08807 USA

Manufactured by:
Bausch & Lomb Incorporated
Tampa, FL 33637 USA
Under license from:
Senju Pharmaceutical Co., Ltd.
Osaka, Japan 541-0046
U.S. Patent Numbers: 8,784,789 and 8,877,168

BEPREVE is a trademark of Bausch & Lomb Incorporated or its affiliates.
© 2022 Bausch & Lomb Incorporated or its affiliates

9291104 (folded)
9291004 (flat)

PACKAGE/LABEL PRINCIPAL DISPLAY PANEL

NDC 24208-629-02

BEPREVE®

(bepotastine besilate
ophthalmic solution) 1.5%

Sterile 5 mL

Rx only
FOR TOPICAL OPHTHALMIC USE

BAUSCH + LOMB

9528502
AB52107